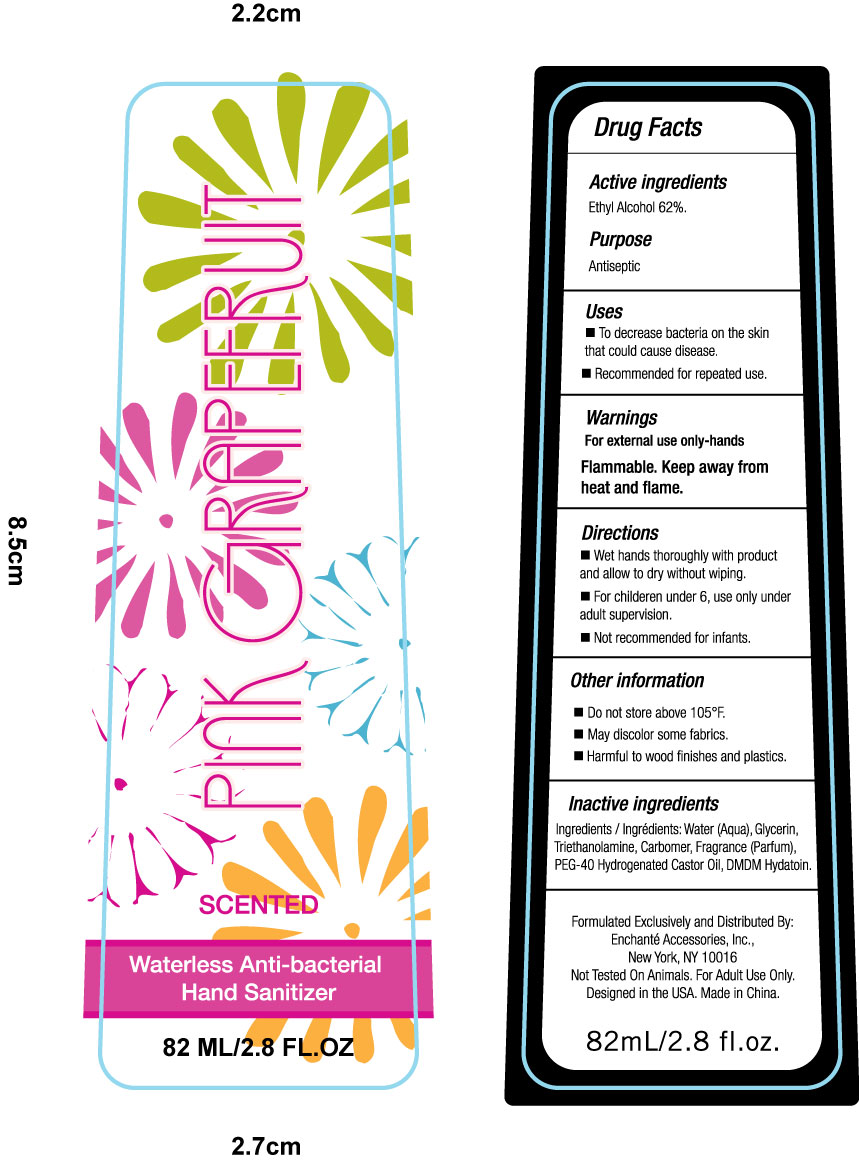 DRUG LABEL: Pink Grape Fruit Waterless Anti-bacterial Hand Sanitizer
NDC: 50593-001 | Form: LIQUID
Manufacturer: Taizhou Xinzhixuan Daily-Use Co., Ltd.
Category: otc | Type: HUMAN OTC DRUG LABEL
Date: 20100203

ACTIVE INGREDIENTS: ALCOHOL 62.000 g/100 g
INACTIVE INGREDIENTS: WATER 35.400 g/100 g; GLYCERIN 1.0 g/100 g; TROLAMINE 0.25 g/100 g; CARBOMER 934 0.25 g/100 g; DMDM HYDANTOIN 0.4 g/100 g; POLYOXYL 40 CASTOR OIL 0.5 g/100 g

Drug Fact

Active Ingredients
Ethyl Alcohol 62%
Purpose
Antisepic

Uses
To decrease bacteria on the skin that could cause disease. Recommended for repeated use

Warnings
For external use only-hands. Flammable. Keep away from heat and flame.

Directions
Wet hands thoroughly with product and allow to dry without wiping.
For children under 6,use only under adult supervision.
Not recommended for infants.

Other Information
Do not store above 105F
May discolor some fabrics.
Harmful to wood finishes and plastics

Inactive Ingredients

water(Aqua), Glycerin, Triethanolamine, Carbomer, Fragrance(parfum), PEG-40 Hydrogenated Castor Oil, DMDM Hydantoin

label